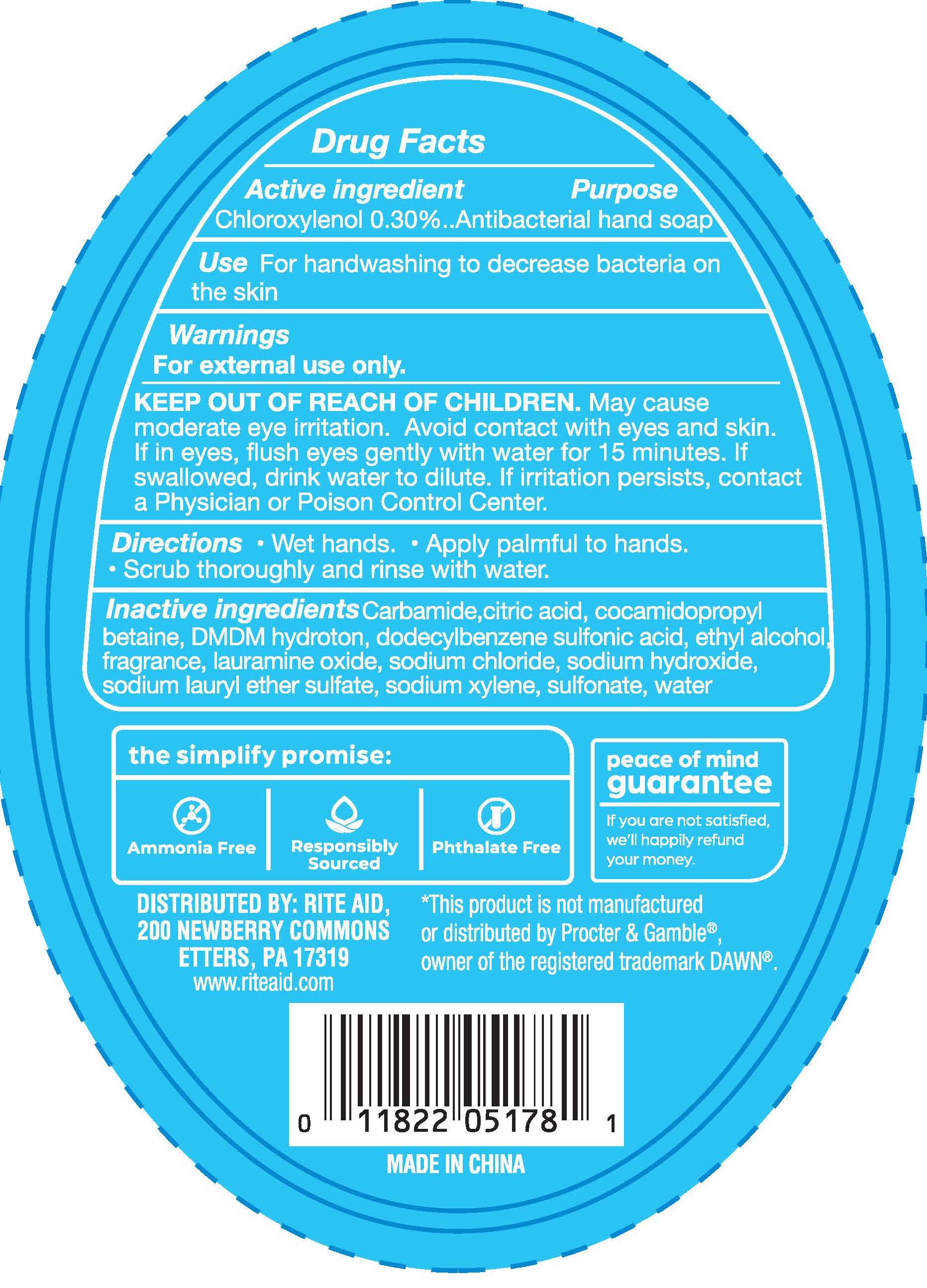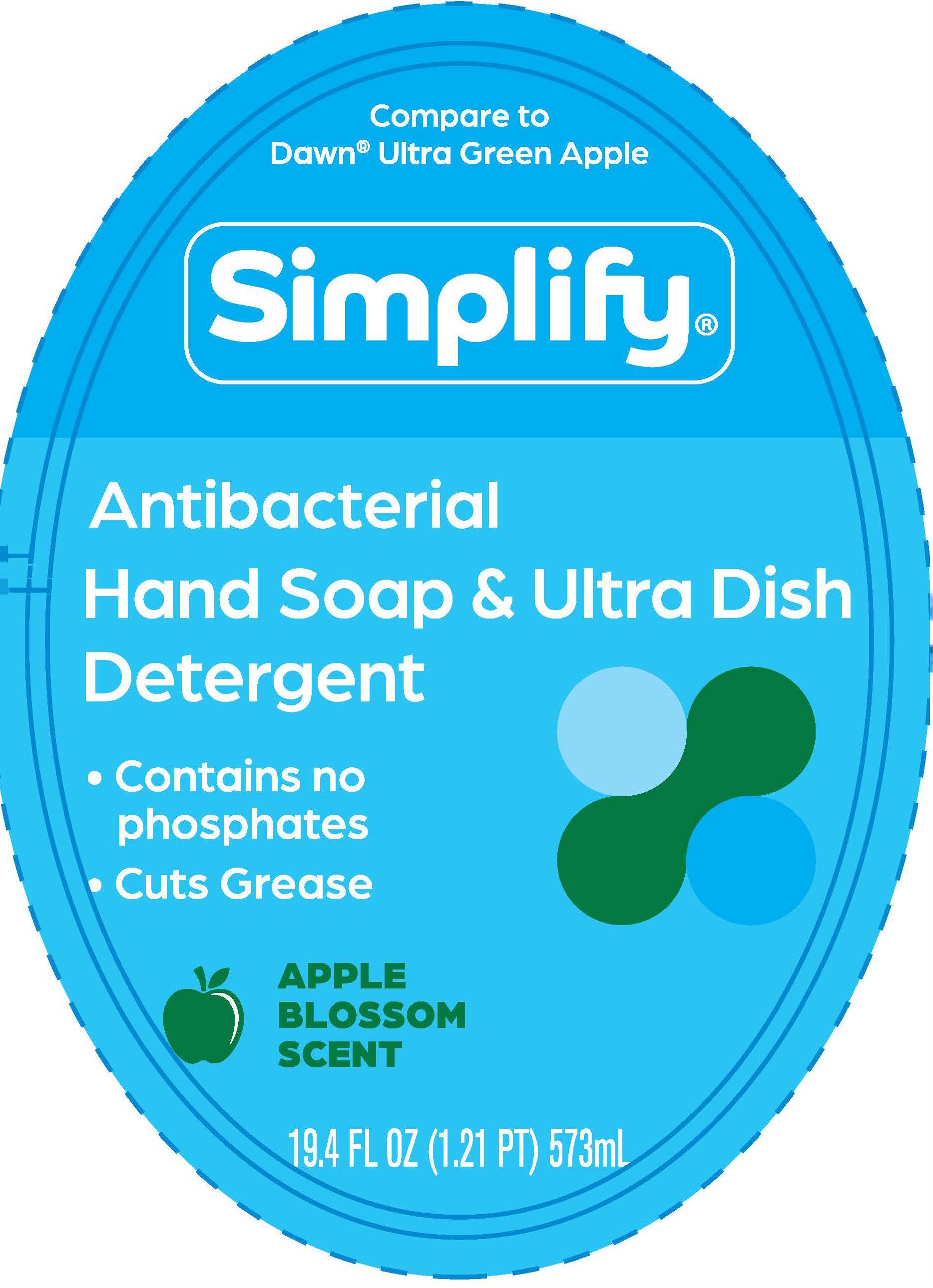 DRUG LABEL: Simplify Antibacterial Hand
NDC: 11822-0281 | Form: SOAP
Manufacturer: Rite Aid Corporation
Category: otc | Type: HUMAN OTC DRUG LABEL
Date: 20251215

ACTIVE INGREDIENTS: CHLOROXYLENOL 0.3 g/100 mL
INACTIVE INGREDIENTS: DMDM HYDANTOIN; LAURAMINE OXIDE; SODIUM HYDROXIDE; ANHYDROUS CITRIC ACID; SODIUM CHLORIDE; DODECYLBENZENESULFONIC ACID; WATER; UREA; SODIUM C12-14 ALKETH-3 SULFATE; ALCOHOL; COCAMIDOPROPYL BETAINE; SODIUM XYLENESULFONATE

Drug Facts

Active Ingredient

Chloroxylenol 0.30%

Purpose

Antibacterial hand soap

Use

For handwashing to decrease bacteria on the skin

Warnings

For external use only

KEEP OUT OF REACH OF CHILDREN.

May cause moderate eye irritation. Avoid contact with eyes and skin. If in eyes, flush eyes gently with water for 15 minutes. If swallowed, drink water to dilute. If irritation persists, contact a Physician or Poison Control Center.

Directions

- Wet hands.
- Apply palmful to hands.
- Scrub thoroughly and rinse with water.

Inactive Ingredients

Carbamide, citric acid, cocamidopropyl betaine, DMDM hydroton, dodecylbenzene sulfonic acid, ethyl alcohol, fragrance, lauramine oxide, sodium chloride, sodium hydroxide, sodium lauryl ether sulfate, sodium xylene sulfonate, water

PACKAGE LABEL

Compare to

Dawn® Ultra Green Apple

Simplify®

Antimicrobial

Hand Soap & Ultra Dish

Detergent

- Contains no

phosphates

- Cuts Grease

APPLE

BLOSSOM

SCENT

19.4 FL OZ (1.21 PT) 573 mL